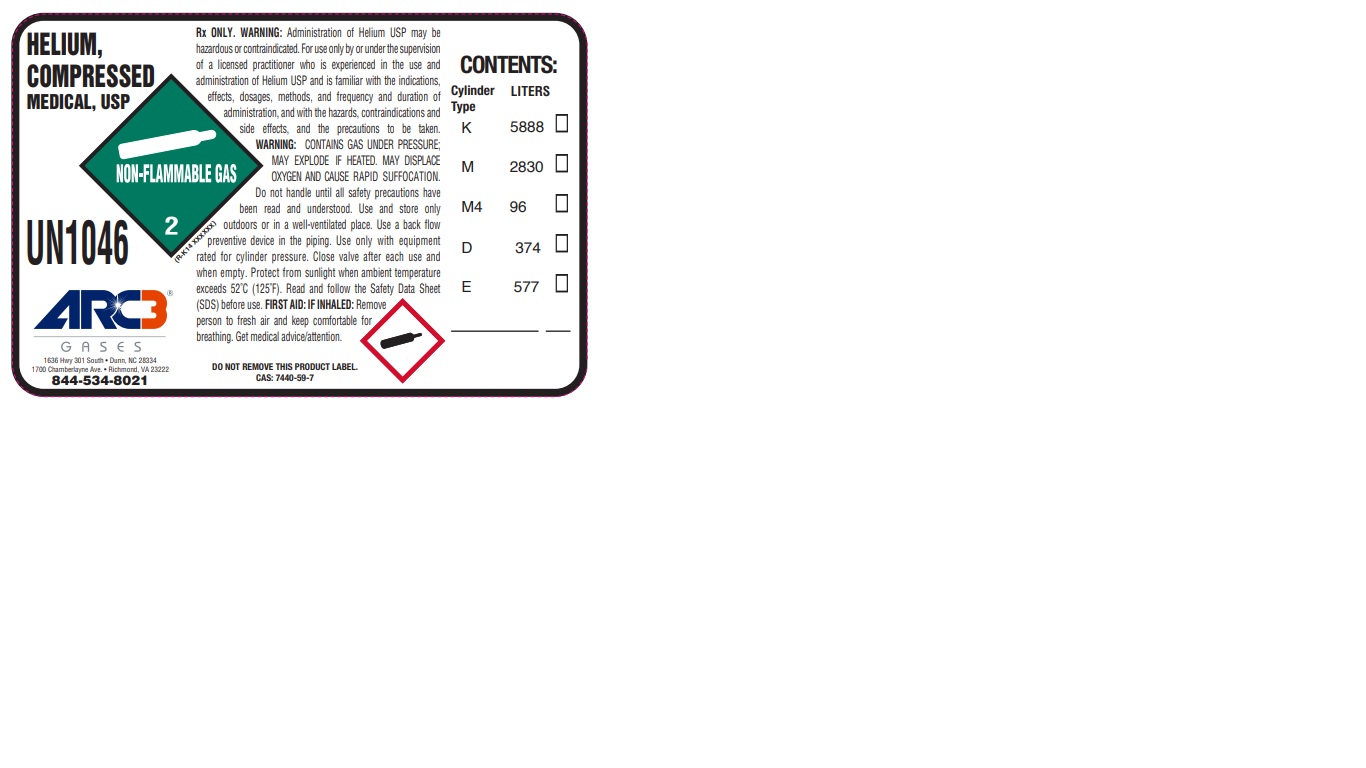 DRUG LABEL: Helium
NDC: 49575-200 | Form: GAS
Manufacturer: Machine & Welding Supply Company dba Arc3 Gases South
Category: prescription | Type: HUMAN PRESCRIPTION DRUG LABEL
Date: 20241206

ACTIVE INGREDIENTS: HELIUM 990 mL/1 L

Helium-200

PACKAGE LABEL

HELIUM, COMPRESSED MEDICAL, USP

UN1046

ARC3 GASES

1636 Hwy 301 South, Dunn, NC 28334

1700 Chamberlayne Ave., Richmond, VA 23222

844-534-8021

Rx ONLY. WARNING: Administration of Helium USP may be hazardous or contraindicated. For use only by or under the supervision of a licensed practitioner who is experienced in the use and administration of Helium USP and is familiar with the indications, effects, dosages, methods, and frequency and duration of administration, and with the hazards, contraindications, and side effects, and the precautions to be taken. WARNING: CONTAINS GAS UNDER PRESSURE; MAY EXPLODE IF HEATED. MAY DISPLACE OXYGEN AND CAUSE RAPID SUFFOCATION. Do not handle until all safety precautions have been read and understood. Use and store only outdoors or in a well-ventilated place. Use a back flow preventive device in the piping. Use only with equipment rated for cylinder pressure. Close valve after each use and when empty. Protect from sunlight when ambient temperature exceeds 52 C (125 F). Read and follow the Safety Data Sheet (SDS) before use. FIRST AID: IF INHALED: Remove person to fresh air and keep comfortable for breathing. Get medical advice/attention.

DO NOT REMOVE THIS PRODUCT LABEL.

CAS: 7440-59-7

CONTENTS:

Cylinder Type LITERS

K 5888

M 2830

M4 96

D 374

E 577